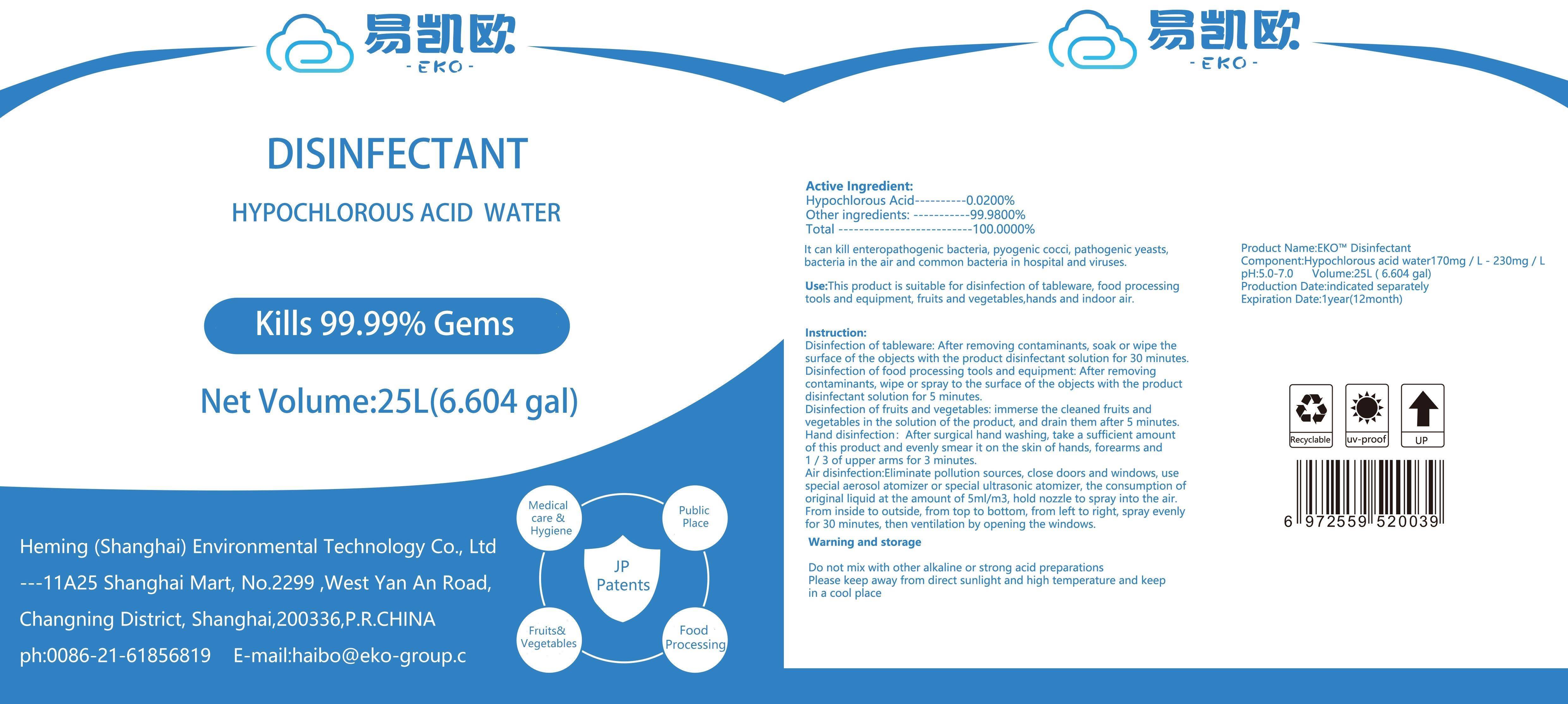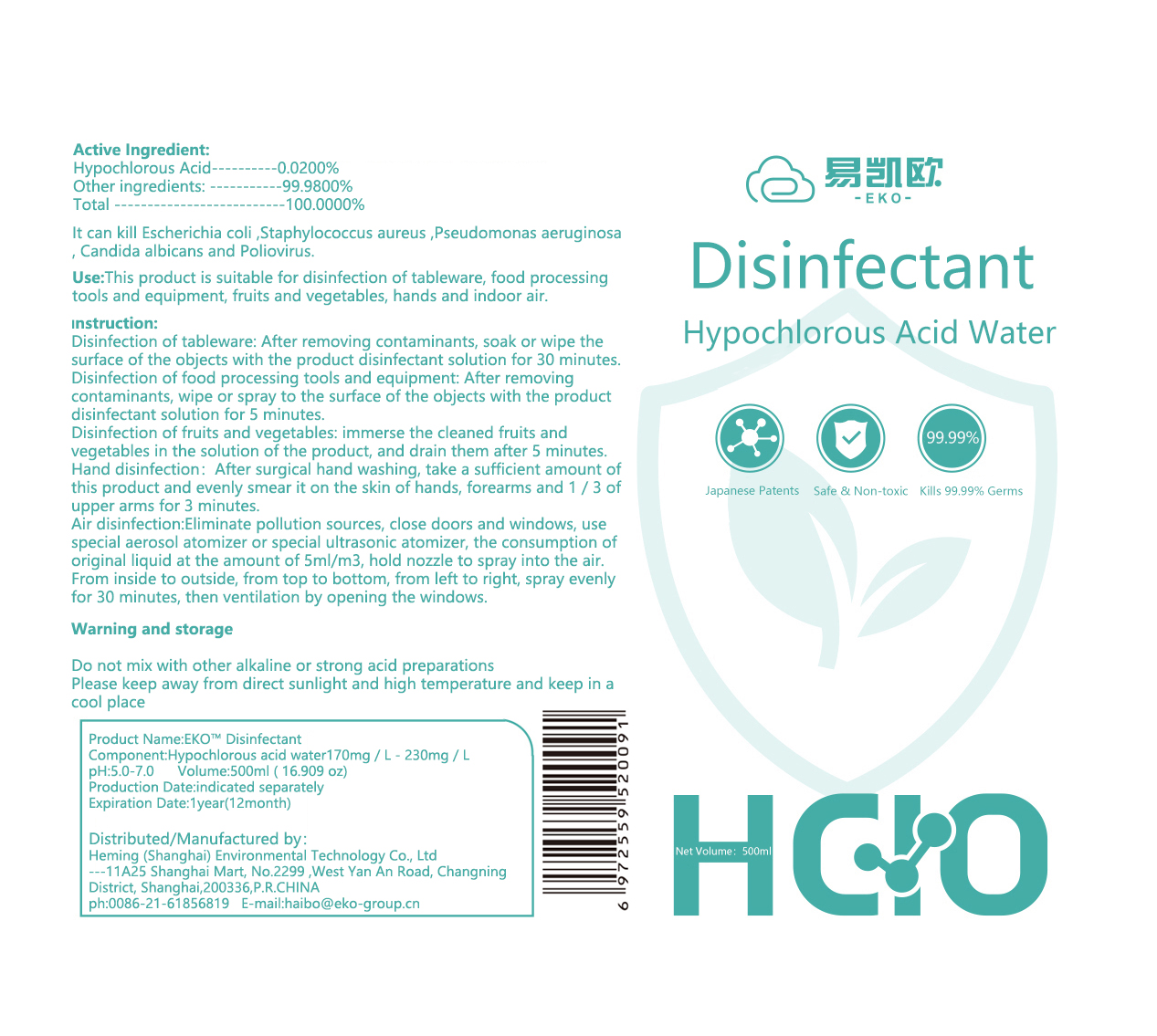 DRUG LABEL: EKO Disinfectant
NDC: 77756-001 | Form: LIQUID
Manufacturer: Heming (Shanghai) Environmental Technology Co., Ltd.
Category: otc | Type: HUMAN OTC DRUG LABEL
Date: 20200512

ACTIVE INGREDIENTS: HYPOCHLOROUS ACID 200 mg/1000 mL
INACTIVE INGREDIENTS: WATER

This is a hand sanitizer manufactured according to the Temporary Policy for Preparation of Certain Alcohol-Based Hand Sanitizer Products During the Public Health Emergency (CoViD-19); Guidance for Industry.

The hand sanitizer is manufactured using only the following United States Pharmacopoeia (USP) grade ingredients in the preparation of the product (percentage in final product formulation) consistent with World Health Organization (WHO) recommendations:

1. HYPOCHLOROUS ACID (0.02%) in an aqueous solution denatured according to Alcohol and Tobacco Tax and Trade Bureau regulations in 27 CFR part 20.
2. Sterile distilled water or boiled cold water.

The firm does not add other active or inactive ingredients. Different or additional ingredients may impact the quality and potency of the product.

Active Ingredient(s)

HYPOCHLOROUS ACID 0.02 %

Purpose

Disinfectant.

Use

This product is suitable for disinfection of tableware, food processing tools and equipment, fruits and vegestables, hands and indoor air.

Warnings

For external use only. Do not mix with other alkaline or strong acid preparations.

Do not use

- in children less than 2 months of age
- on open skin wounds

When using this product keep out of eyes, ears, and mouth. In case of contact with eyes, rinse eyes thoroughly with water.
Stop use and ask a doctor if irritation or rash occurs. These may be signs of a serious condition.
Keep out of reach of children. If swallowed, get medical help or contact a Poison Control Center right away.

Stop use and ask a doctor if irritation or rash occurs. These may be signs of a serious condition.

Keep out of reach of children. If swallowed, get medical help or contact a Poison Control Center right away.

Directions

- Place enough product on hands to cover all surfaces. Rub hands together until dry.
- Supervise children under 6 years of age when using this product to avoid swallowing.

Other information

- Store between 15-30C (59-86F)
- Avoid freezing and excessive heat above 40C (104F)
- Please keep away from direct sunlight and high temperature and keep in a cool place

Inactive ingredients

purified water USP

Package Label - Principal Display Panel

30ml NDC: 77756-001-01